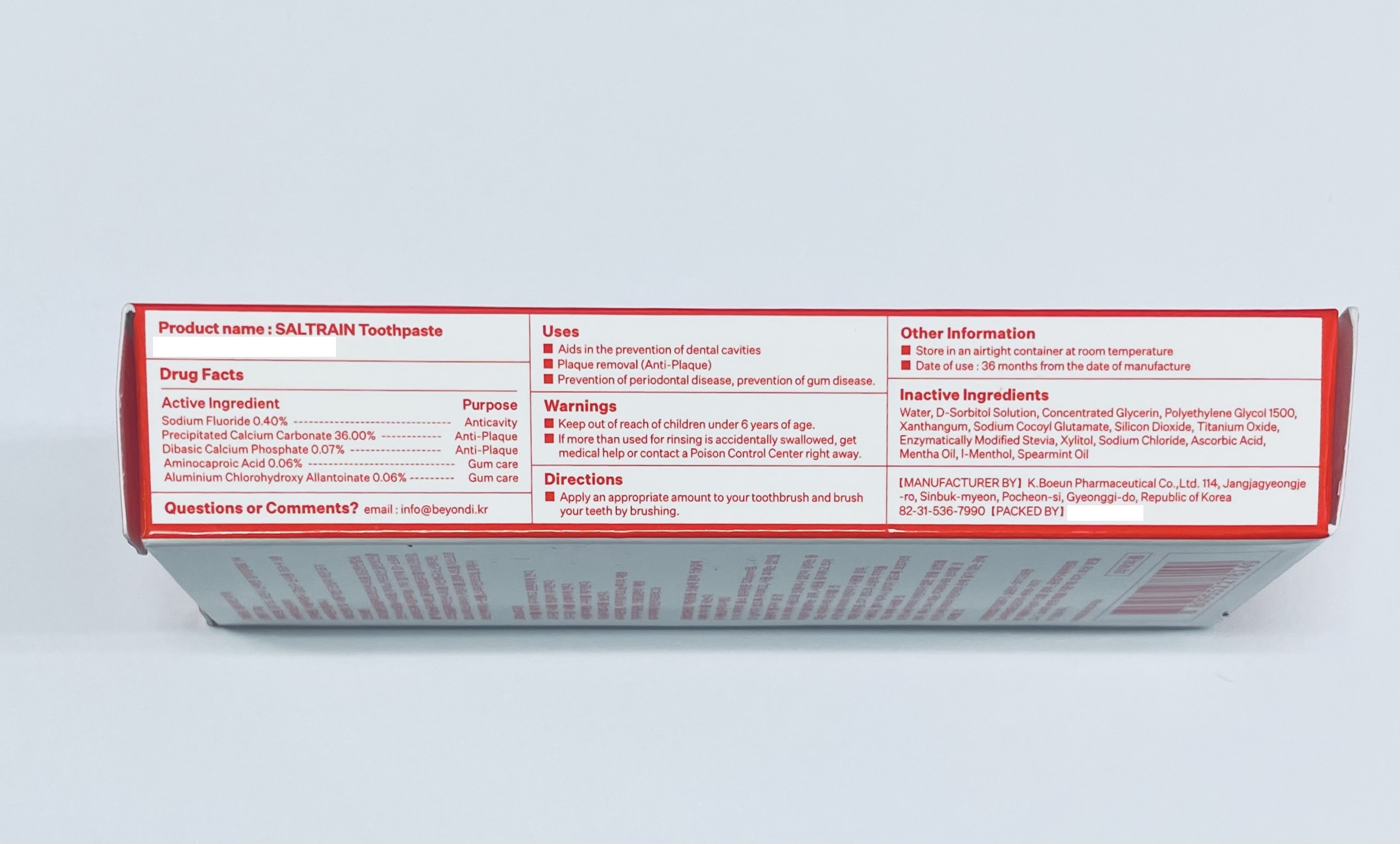 DRUG LABEL: SALTRAIN TOOTH
NDC: 74724-0029 | Form: PASTE, DENTIFRICE
Manufacturer: K.Boeun Pharmaceutical Co.,Ltd.
Category: otc | Type: HUMAN OTC DRUG LABEL
Date: 20211130

ACTIVE INGREDIENTS: SODIUM MONOFLUOROPHOSPHATE 0.4 g/100 g; CALCIUM PHOSPHATE, DIBASIC, ANHYDROUS 0.07 g/100 g; CALCIUM CARBONATE 36 g/100 g; ALCLOXA 0.06 g/100 g; AMINOCAPROIC ACID 0.06 g/100 g
INACTIVE INGREDIENTS: XYLITOL; WATER

ACTIVE INGREDIENT

Sodium Monofluorophosphate, Precipitated Calcium Carbonate, Dibasic Calcium Phosphate, Aminocaproic Acid, Aluminium Chlorohydroxy Allantoinate

INACTIVE INGREDIENT

D-Sorbitol Solution
Concentrated Glycerin
Polyethylene Glycol 1500
Xanthangum
Sodium Cocoyl Glutamate
Silicon Dioxide
Titanium Oxide
Enzymatically Modified Stevia

Xylitol
Sodium Chloride

Ascorbic Acid
Mentha Oil

l-Menthol
Spearmint Oil
Water

PURPOSE

For dental care

Keep out of reach of children

INDICATIONS AND USAGE

Apply an appropriate amount to your toothbrush and brush your teeth by brushing.

Warnings

Keep out of reach of children

■ If more than used for rinsing is accidentally swallowed, get medical help or contact a Poison Control Center right away.

Other Information

■ Store in an airtight container at room temperature

■ Date of use : 36 months from the date of manufacture

DOSAGE AND ADMINISTRATION

For dental use only